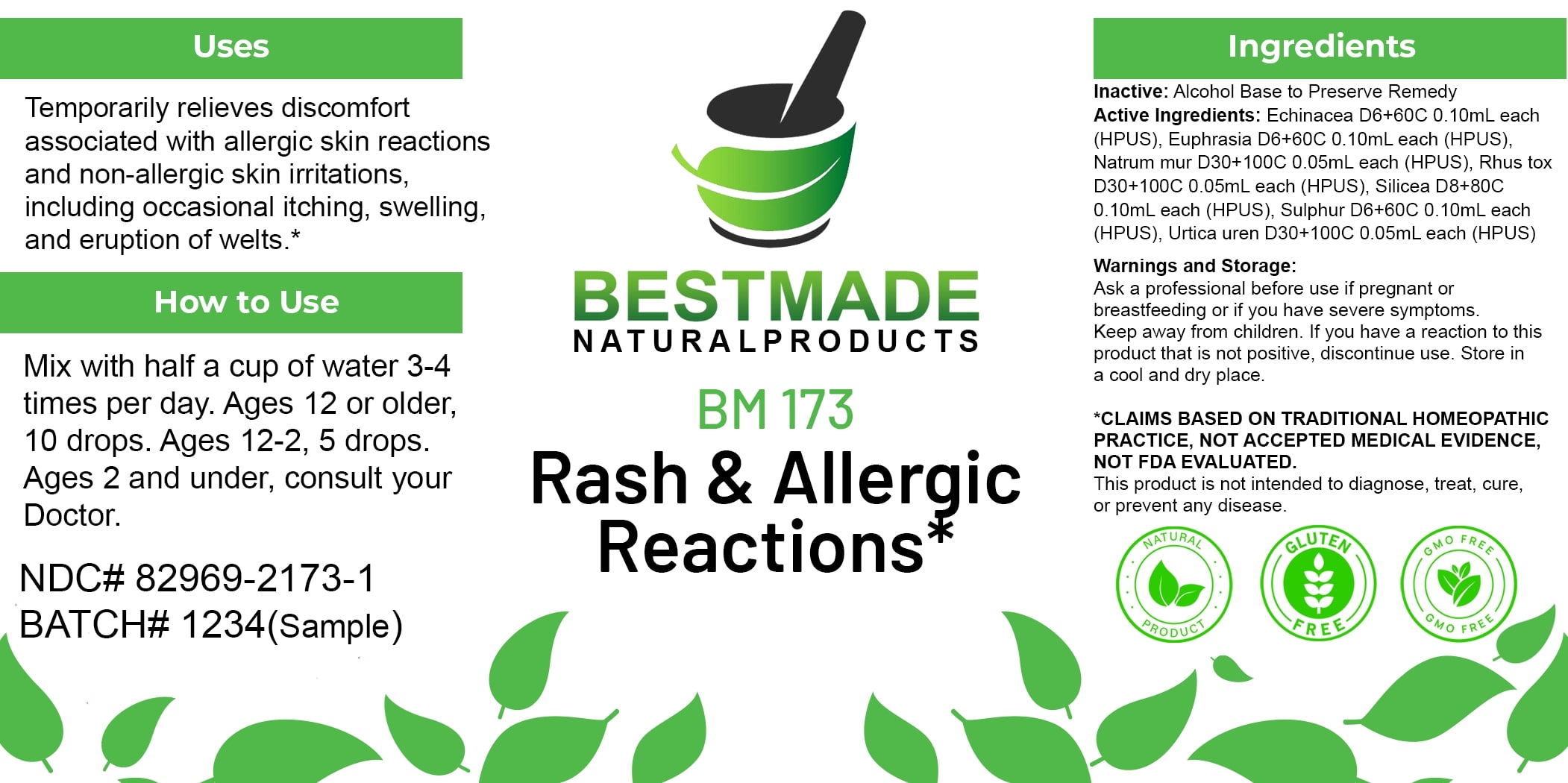 DRUG LABEL: Bestmade Natural Products BM173
NDC: 82969-2173 | Form: LIQUID
Manufacturer: Bestmade Natural Products
Category: homeopathic | Type: HUMAN OTC DRUG LABEL
Date: 20250219

ACTIVE INGREDIENTS: EUPHRASIA STRICTA 30 [hp_C]/30 [hp_C]; TOXICODENDRON PUBESCENS LEAF 30 [hp_C]/30 [hp_C]; ECHINACEA, UNSPECIFIED 30 [hp_C]/30 [hp_C]; URTICA URENS 30 [hp_C]/30 [hp_C]; SULFUR 30 [hp_C]/30 [hp_C]; SODIUM CHLORIDE 30 [hp_C]/30 [hp_C]; SILICA 30 [hp_C]/30 [hp_C]
INACTIVE INGREDIENTS: ALCOHOL 30 [hp_C]/30 [hp_C]

BM173

DOSAGE AND ADMINISTRATION

How to Use

Mix with half a cup of water 3-4 times per day. Ages 12 or older, 10 drops. Ages 12-2, 5 drops. Ages 2 and under, consult your Doctor.

INACTIVE INGREDIENT

Ingredients

Inactive: Alcohol Base to Preserve Remedy

ACTIVE INGREDIENT

Active Ingredients: Echinacea D6+60C 0.10ml each (HPUS), Euphrasia D6+60C 0.10ml each (HPUS), Natrum mur D30+100C 0.05ml each (HPUS), Rhus tox D30+100C 0.05ml each (HPUS), Silicea D6+60C 0.10ml each (HPUS), Sulphur D6+60C 0.10ml each (HPUS), Urtica urens D30+100C 0.05ml each (HPUS)

Uses

Temporarily relieves discomfort associated with allergic skin reactions and non-allergic skin irritations, including occasional itching, swelling, and eruption of welts.*

*CLAIMS BASED ON TRADITIONAL HOMEOPATHIC PRACTICE. NOT ACCEPTED MEDICAL EVIDENCE. NOT FDA EVALUATED.

This product is not intended to diagnose, treat, cure, or prevent any disease.

Uses

Temporarily relieves discomfort associated with allergic skin reactions and non-allergic skin irritations, including occasional itching, swelling, and eruption of welts.*

*CLAIMS BASED ON TRADITIONAL HOMEOPATHIC PRACTICE. NOT ACCEPTED MEDICAL EVIDENCE. NOT FDA EVALUATED.

This product is not intended to diagnose, treat, cure, or prevent any disease.

KEEP OUT OF REACH OF CHILDREN

Warnings and Storage:

Ask a professional before use if pregnant or breastfeeding or if you have severe symptoms. Keep away from children. If you have a reaction to this product that is not positive, discontinue use. Store in a cool and dry place.

Warnings and Storage:

Ask a professional before use if pregnant or breastfeeding or if you have severe symptoms. Keep away from children. If you have a reaction to this product that is not positive, discontinue use. Store in a cool and dry place.

*CLAIMS BASED ON TRADITIONAL HOMEOPATHIC PRACTICE. NOT ACCEPTED MEDICAL EVIDENCE. NOT FDA EVALUATED.

This product is not intended to diagnose, treat, cure, or prevent any disease.

Entire package label